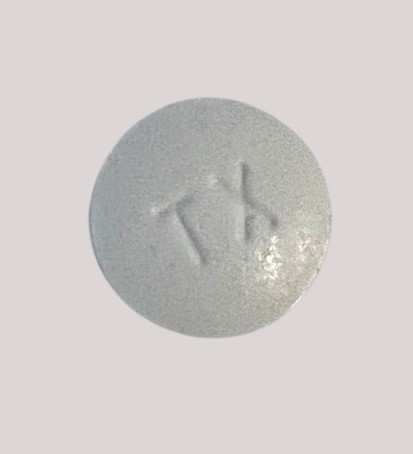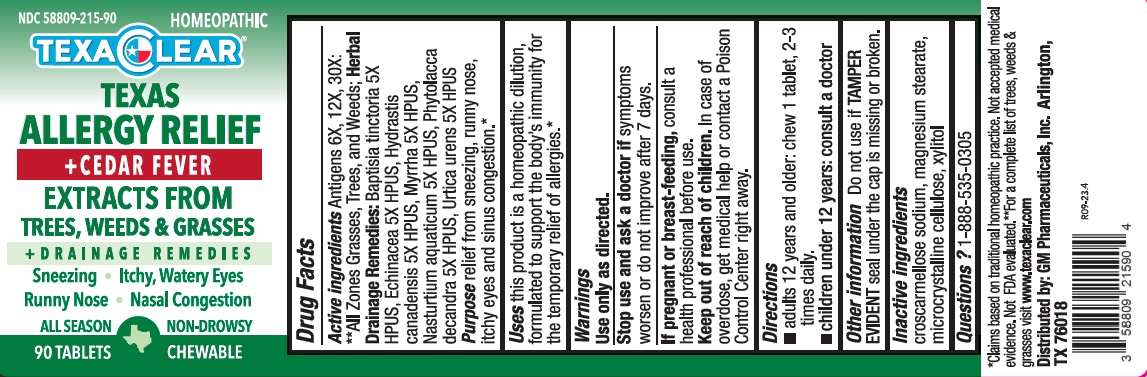 DRUG LABEL: TexaClear Texas Allergy Relief plus Cedar Fever
NDC: 58809-215 | Form: TABLET, CHEWABLE
Manufacturer: GM Pharmaceuticals, INC
Category: homeopathic | Type: HUMAN OTC DRUG LABEL
Date: 20251209

ACTIVE INGREDIENTS: SOLIDAGO CANADENSIS POLLEN 6 [hp_X]/1 min; PHYTOLACCA AMERICANA ROOT 5 [hp_X]/1 min; AMBROSIA ARTEMISIIFOLIA POLLEN 6 [hp_X]/1 min; POPULUS DELTOIDES SUBSP. MONILIFERA POLLEN 6 [hp_X]/1 min; PINUS ECHINATA POLLEN 6 [hp_X]/1 min; SORGHUM HALEPENSE POLLEN 6 [hp_X]/1 min; QUERCUS MACROCARPA POLLEN 6 [hp_X]/1 min; QUERCUS NIGRA POLLEN 6 [hp_X]/1 min; OLEA EUROPAEA POLLEN 6 [hp_X]/1 min; BROUSSONETIA PAPYRIFERA POLLEN 6 [hp_X]/1 min; ARTEMISIA VULGARIS POLLEN 6 [hp_X]/1 min; POPULUS NIGRA POLLEN 6 [hp_X]/1 min; AMBROSIA PSILOSTACHYA POLLEN 6 [hp_X]/1 min; QUERCUS RUBRA POLLEN 6 [hp_X]/1 min; SECALE CEREALE POLLEN 6 [hp_X]/1 min; CARYA OVATA POLLEN 6 [hp_X]/1 min; RUMEX ACETOSELLA POLLEN 6 [hp_X]/1 min; AMARANTHUS TUBERCULATUS POLLEN 6 [hp_X]/1 min; RUMEX CRISPUS POLLEN 6 [hp_X]/1 min; CELTIS OCCIDENTALIS POLLEN 6 [hp_X]/1 min; PLANTAGO LANCEOLATA POLLEN 6 [hp_X]/1 min; POPULUS DELTOIDES SUBSP. DELTOIDES POLLEN 6 [hp_X]/1 min; AMBROSIA ACANTHICARPA POLLEN 6 [hp_X]/1 min; CHENOPODIUM ALBUM POLLEN 6 [hp_X]/1 min; BAPTISIA TINCTORIA ROOT 5 [hp_X]/1 min; TAXODIUM DISTICHUM POLLEN 6 [hp_X]/1 min; JUGLANS NIGRA POLLEN 6 [hp_X]/1 min; ECHINACEA ANGUSTIFOLIA ROOT 5 [hp_X]/1 min; MYRRH 5 [hp_X]/1 min; ULMUS AMERICANA POLLEN 6 [hp_X]/1 min; GOLDENSEAL 5 [hp_X]/1 min; EUPATORIUM CAPILLIFOLIUM POLLEN 6 [hp_X]/1 min; PROSOPIS JULIFLORA POLLEN 6 [hp_X]/1 min; MORUS ALBA POLLEN 6 [hp_X]/1 min; SYAGRUS ROMANZOFFIANA POLLEN 6 [hp_X]/1 min; AMBROSIA CONFERTIFLORA POLLEN 6 [hp_X]/1 min; FRAXINUS AMERICANA POLLEN 6 [hp_X]/1 min; CYCLACHAENA XANTHIFOLIA POLLEN 6 [hp_X]/1 min; URTICA DIOICA POLLEN 6 [hp_X]/1 min; CARYA ILLINOINENSIS POLLEN 6 [hp_X]/1 min; PINUS STROBUS POLLEN 6 [hp_X]/1 min; AMBROSIA BIDENTATA POLLEN 6 [hp_X]/1 min; ARTEMISIA TRIDENTATA POLLEN 6 [hp_X]/1 min; XANTHIUM STRUMARIUM POLLEN 6 [hp_X]/1 min; JUNIPERUS VIRGINIANA POLLEN 6 [hp_X]/1 min; BETULA NIGRA POLLEN 6 [hp_X]/1 min; PLATANUS OCCIDENTALIS POLLEN 6 [hp_X]/1 min; ACER SACCHARUM POLLEN 6 [hp_X]/1 min; EUCALYPTUS GLOBULUS POLLEN 6 [hp_X]/1 min; MYRICA CERIFERA POLLEN 6 [hp_X]/1 min; SCHINUS MOLLE POLLEN 6 [hp_X]/1 min; BASSIA SCOPARIA POLLEN 6 [hp_X]/1 min; POA PRATENSIS POLLEN 6 [hp_X]/1 min; QUERCUS VIRGINIANA POLLEN 6 [hp_X]/1 min; JUNIPERUS ASHEI POLLEN 6 [hp_X]/1 min; MELALEUCA QUINQUENERVIA POLLEN 6 [hp_X]/1 min; QUERCUS GAMBELII POLLEN 6 [hp_X]/1 min; QUERCUS STELLATA POLLEN 6 [hp_X]/1 min; QUERCUS ALBA POLLEN 6 [hp_X]/1 min; AMARANTHUS RETROFLEXUS POLLEN 6 [hp_X]/1 min; LIGUSTRUM VULGARE POLLEN 6 [hp_X]/1 min; AMBROSIA TRIFIDA POLLEN 6 [hp_X]/1 min; MORUS RUBRA POLLEN 6 [hp_X]/1 min; SALSOLA KALI POLLEN 6 [hp_X]/1 min; ATRIPLEX WRIGHTII POLLEN 6 [hp_X]/1 min; DISTICHLIS SPICATA POLLEN 6 [hp_X]/1 min; AMARANTHUS SPINOSUS POLLEN 6 [hp_X]/1 min; ANTHOXANTHUM ODORATUM POLLEN 6 [hp_X]/1 min; LIQUIDAMBAR STYRACIFLUA POLLEN 6 [hp_X]/1 min; HOLCUS LANATUS POLLEN 6 [hp_X]/1 min; JUNIPERUS OCCIDENTALIS POLLEN 6 [hp_X]/1 min; POPULUS ALBA POLLEN 6 [hp_X]/1 min; SALIX NIGRA POLLEN 6 [hp_X]/1 min; URTICA URENS WHOLE 5 [hp_X]/1 min; HESPEROCYPARIS ARIZONICA POLLEN 6 [hp_X]/1 min; PASPALUM NOTATUM POLLEN 6 [hp_X]/1 min; FAGUS GRANDIFOLIA POLLEN 6 [hp_X]/1 min; ACER NEGUNDO POLLEN 6 [hp_X]/1 min; AMARANTHUS PALMERI POLLEN 6 [hp_X]/1 min; AVENA SATIVA POLLEN 6 [hp_X]/1 min; ACACIA DEALBATA POLLEN 6 [hp_X]/1 min; FRAXINUS VELUTINA POLLEN 6 [hp_X]/1 min; ZEA MAYS POLLEN 6 [hp_X]/1 min; TRITICUM AESTIVUM POLLEN 6 [hp_X]/1 min; NASTURTIUM OFFICINALE 5 [hp_X]/1 min
INACTIVE INGREDIENTS: CROSCARMELLOSE SODIUM; XYLITOL; MAGNESIUM STEARATE; MICROCRYSTALLINE CELLULOSE 102

TexaClear Texas Allergy Relief plus Cedar Fever (Homeopathic)

Active Ingredients

Antigens 6X, 12X, 30X: **All Zones Grasses, Trees, and Weeds; Herbal Drainage Remedies: Baptisia tinctoria 5X HPUS, Echinacea 5X HPUS, Hydrastis canadensis 5X HPUS, Myrrha 5X HPUS, Nasturtium aquaticum 5X HPUS, Phytolacca decandra 5X HPUS, Urtica urens 5X HPUS

Purpose

Relief from sneezing, runny nose, itchy eyes and sinus congestion.*

Uses

This product is a homeopathic dilution, formulated to support the body's immunity for the temporary relief of allergies.*

Warnings

Use only as directed.

Stop use and ask a doctor if

symptoms worsen or do not improve after 7 days.

If pregnant or breast-feeding,

consult a health professional before use.

Keep out of reach of children.

In case of overdose, get medical help or contact a Poison Control Center right away.

Directions

- Adults 12 years and older: chew 1 tablet, 2-3 times daily
- Children under 12 years: consult a doctor

Other information

Do not use if TAMPER EVIDENT seal under the cap is missing or broken.

Inactive ingredients

croscarmellose sodium, magnesium stearate, microcrystalline cellulose, xylitol

Questions?

1-888-535-0305

HEALTH CLAIM

* Claims based on traditional homeopathic practice. Not accepted medical evidence. Not FDA evaluated.

** For a complete list of trees, weeds & grasses visit www.texaclear.com

Distributed by: GM Pharmaceuticals, Inc. Arlington, TX 76018

NDC 588809-215-90

HOMEOPATHIC

TEXACLEAR

TEXAS

ALLERGY RELIEF

+ CEDAR FEVER

EXTRACTS FROM

TREES, WEEDS, & GRASSES

+ DRAINAGE REMEDIES

Sneezing Itchy, Watery Eyes

Runny Nose Nasal Congestion

ALL SEASON NON-DROWSY

90 TABLETS CHEWABLE